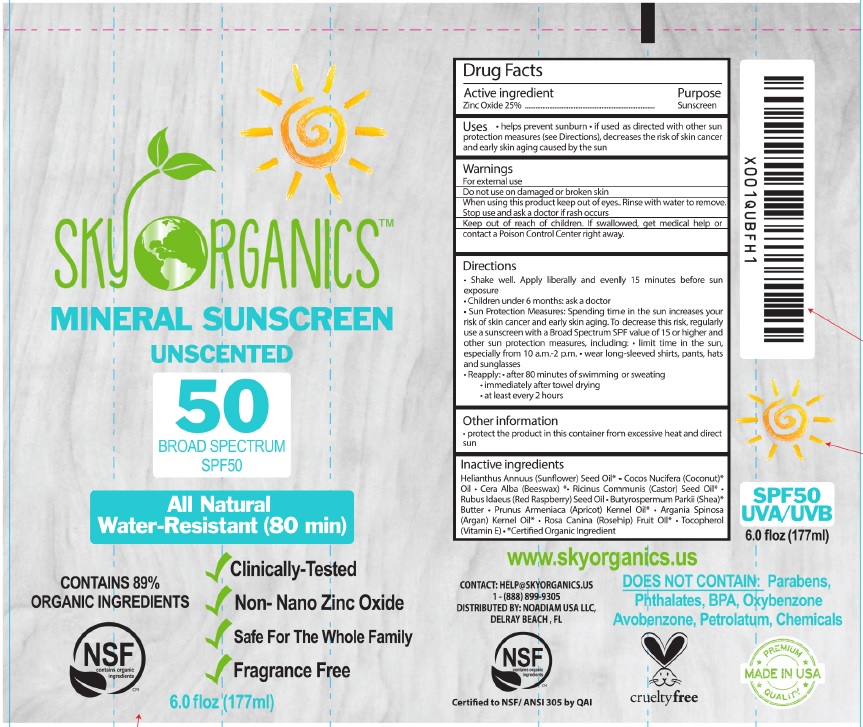 DRUG LABEL: SUNSCREEN
NDC: 62932-185 | Form: OINTMENT
Manufacturer: Private Label Select Ltd CO
Category: otc | Type: HUMAN OTC DRUG LABEL
Date: 20181129

ACTIVE INGREDIENTS: ZINC OXIDE 25 g/100 g
INACTIVE INGREDIENTS: ARGAN OIL; APRICOT KERNEL OIL; HELIANTHUS ANNUUS SEED WAX; CASTOR OIL; YELLOW WAX; COCONUT OIL; SHEA BUTTER; TOCOPHEROL; RASPBERRY SEED OIL; ROSA CANINA FRUIT OIL

Sky Organics Mineral Sunscreen SPF50 177g